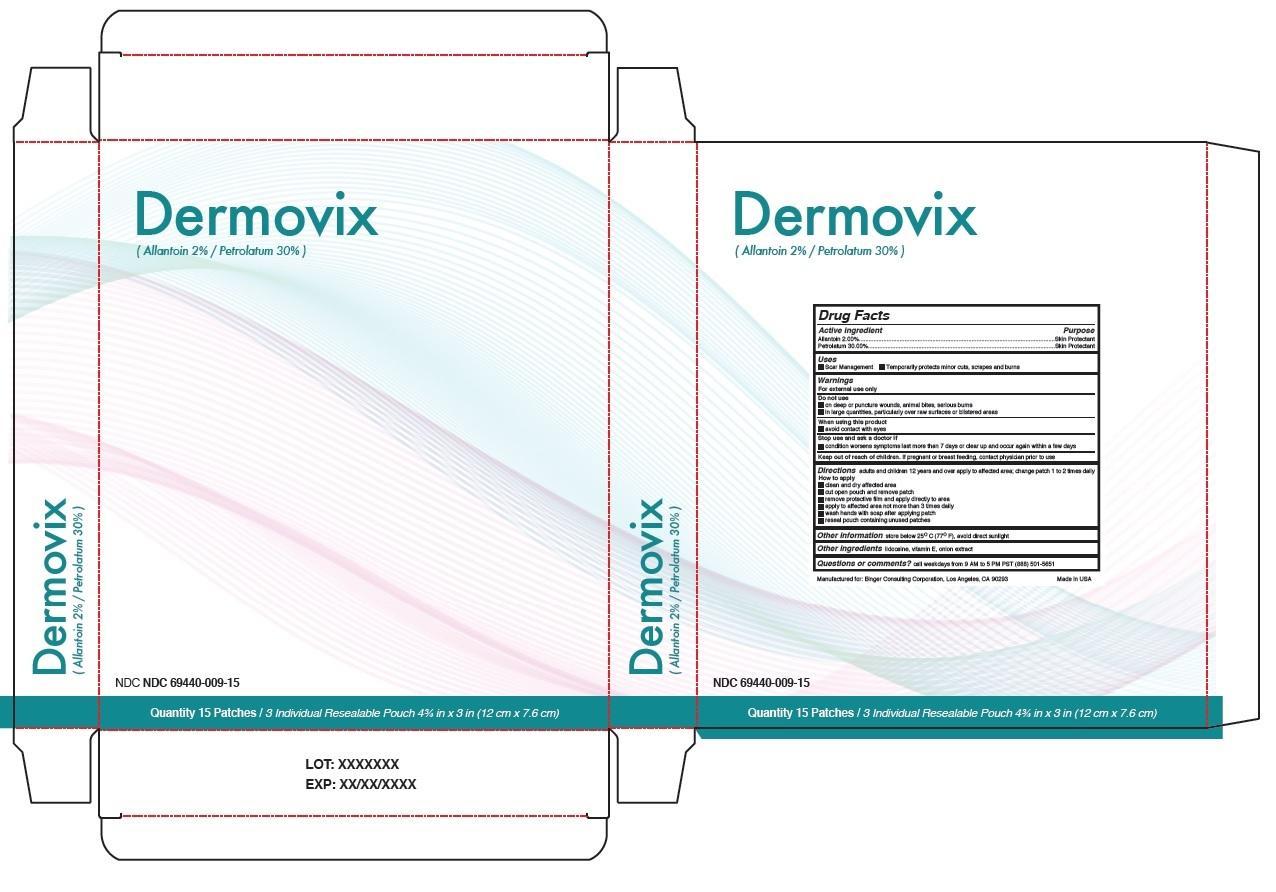 DRUG LABEL: Dermovix
NDC: 69440-009 | Form: PATCH
Manufacturer: Binger Consulting Corporation
Category: otc | Type: HUMAN OTC DRUG LABEL
Date: 20241127

ACTIVE INGREDIENTS: ALLANTOIN 2 g/100 g; PETROLATUM 30 g/100 g
INACTIVE INGREDIENTS: LIDOCAINE; .ALPHA.-TOCOPHEROL; ONION

Dermovix

Active ingredient

Allantoin 2.00%

Petrolatum 30.00%

Purpose

Skin Protectant

Skin Protectant

Keep out of reach of children. If pregnant or breast feeding, contact physician prior to use.

Uses

• Scar Management • Temporarily protects minor cuts, scrapes and burns

Warnings

For external use only

Do not use

• on deep or puncture wounds, animal bites, serious burns

• in large quantities, particularly over raw surfaces or blistered areas

When using this product

• avoid contact with eyes

Stop use and ask a doctor if

• condition worsens symptoms last more than 7 days or clear up and occur again within a few days

DOSAGE AND ADMINISTRATION

Directions adults and children 12 years and over apply to affected area; change patch 1 to 2 times daily

How to apply

• clean and dry affected area

• cut open pouch and remove patch

• remove protective film and apply directly to area

• apply to affected area not more than 3 times daily

• wash hands with soap after applying patch

• reseal pouch containing unused patches

INACTIVE INGREDIENT

Other ingredients lidocaine, vitamin E, onion extract

Questions or comments? call weekdays from 9 AM to 5 PM PST (888) 501-5651

Other information store below 25°C (77° F), avoid direct sunlight